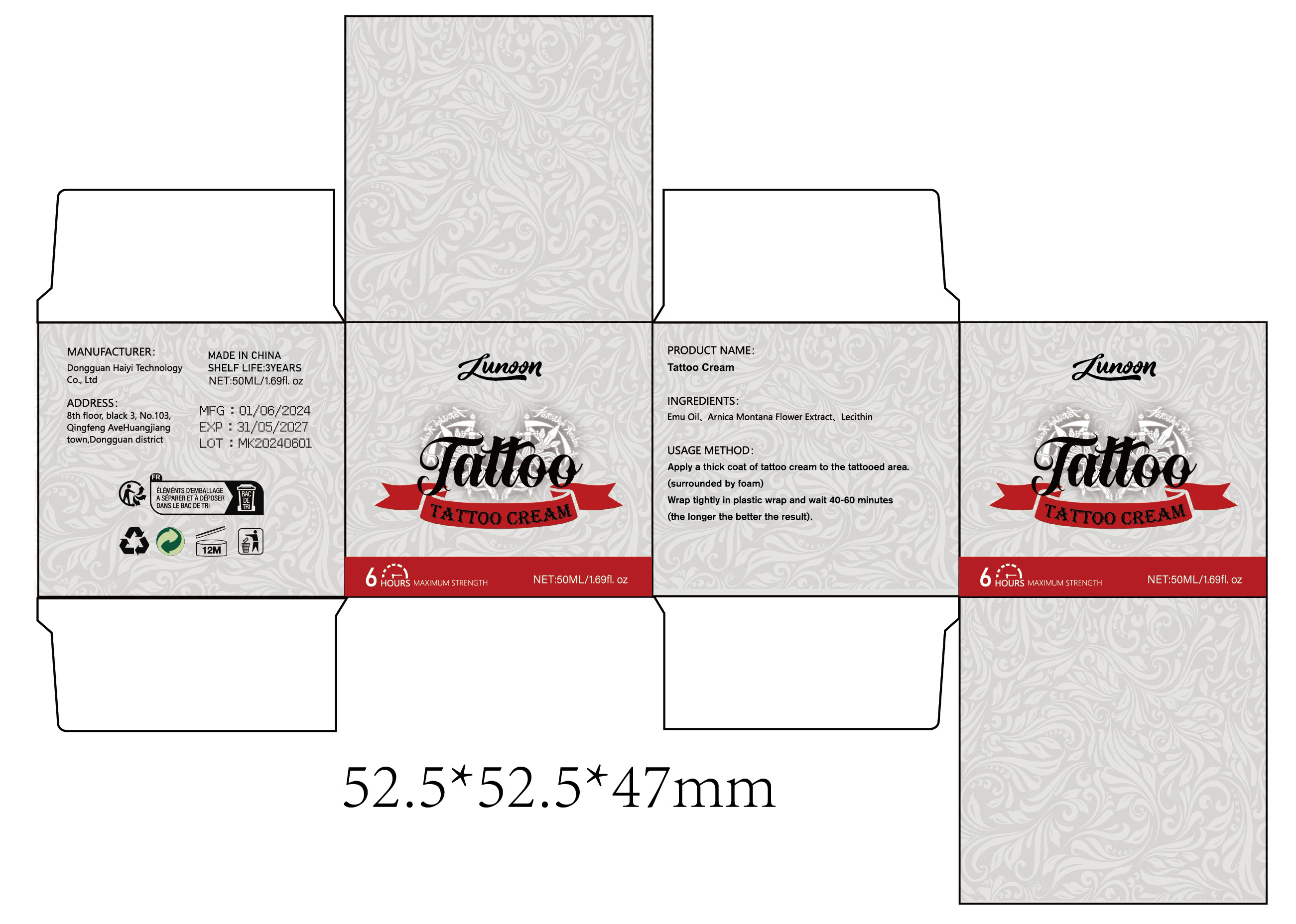 DRUG LABEL: Tattoo Cream
NDC: 84732-036 | Form: CREAM
Manufacturer: Dongguan Haiyi Technology Co.,Ltd.
Category: otc | Type: HUMAN OTC DRUG LABEL
Date: 20241009

ACTIVE INGREDIENTS: EMU OIL 1 mg/100 mL
INACTIVE INGREDIENTS: ARNICA MONTANA FLOWER; SOYBEAN LECITHIN

Active ingredient

Emu Oil

Inactive ingredient

Arnica Montana Flower Extract、Lecithin

Purpose section

Enjoy a painless tattoo

Warning

1).For external use only, avoid directcontact with eyes, lf you feel any
discomfort, stop using itand wash it with plenty of water. In severe cases,
pleaseseek medical attention in time.
2). Not allowed to be used ondamaged skin,

stop use

This product may cause allergic reactions in asmall number of people.
lf youexperience any discomfort,please stop using it immediately.

not use

Not suitable for use by children, pregnantor breast feeding people.

OUT OF CHILDREN

KEEP THE PRODUCT OUT OF REACH OF CHILDREN to

HOW TO USE

Apply a thick coat of tattoo cream to the tattooed area.
(surrounded by foam)
Wrap tightly in plastic wrap and wait 40-60 minutes

(the longer the better the result).

Dosage

Apply to the area where you want to get tattooed before tattooing and wrap for 40-60 minutes